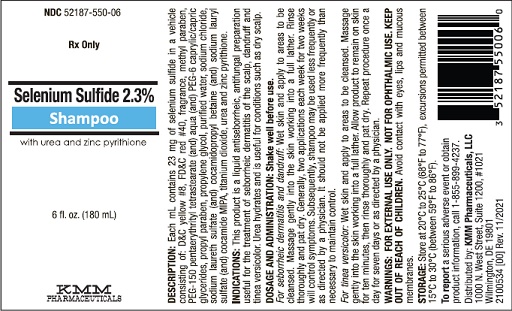 DRUG LABEL: SELENIUM SULFIDE
NDC: 52187-550 | Form: SHAMPOO
Manufacturer: KMM Pharmaceuticals, LLC
Category: prescription | Type: HUMAN PRESCRIPTION DRUG LABEL
Date: 20251218

ACTIVE INGREDIENTS: SELENIUM SULFIDE 23 mg/1 mL

Selenium Sulfide 2.3% Shampoo

Rx Only
FOR EXTERNAL USE ONLY. NOT FOR OPHTHALMIC USE.

DESCRIPTION:

Each mL contains 23 mg of selenium sulfide in a vehicle consisting of: D&C yellow #8, FD&C red #40, fragrance, methyl paraben, PEG-150 pentaerythrityl tetrastearate (and) aqua (and) PEG-6 caprylic/capric glycerides, propyl paraben, propylene glycol, purified water, sodium chloride, sodium laureth sulfate (and) cocamidopropyl betaine (and) sodium lauryl sulfate (and) cocamide MIPA, titanium dioxide, urea and zinc pyrithione.

CLINICAL PHARMACOLOGY:

Selenium sulfide appears to have a cytostatic effect on cells of the epidermis and follicular epithelium, reducing corneocyte production.

Pharmacokinetics: The mechanism of action of topically applied selenium sulfide is not yet known.

INDICATIONS:

This product is a liquid antiseborrheic, antifungal preparation useful for the treatment of seborrheic dermatitis of the scalp, dandruff and tinea versicolor. Urea hydrates and is useful for conditions such as dry scalp.

CONTRAINDICATIONS:

This product is contraindicated in persons with known or suspected hypersensitivity to any of the ingredients of the product.

WARNINGS:

KEEP OUT OF REACH OF CHILDREN.

PRECAUTIONS:

FOR EXTERNAL USE ONLY. NOT FOR OPHTHALMIC USE.

General: This product is to be used as directed by a physician and should not be used to treat any condition other than that for which it was prescribed. If redness or irritation occurs, discontinue use and consult a physician.

Information for Patients: Patients should discontinue the use of this product if the condition becomes worse or if a rash develops in the area being treated or elsewhere. Avoid contact with eyes, lips and mucous membranes.

Carcinogenesis, Mutagenesis and Impairment of Fertility: Dermal application of 25% and 50% solutions of 2.5% selenium sulfide lotion on mice over an 88-week period indicated no carcinogenic effects. Studies on reproduction and fertility also have not been performed.

Pregnancy: Category C. Animal reproduction studies have not been conducted with this product. It is also not known whether this product can affect reproduction capacity or cause fetal harm when administered to a pregnant woman. This product should be used by a pregnant woman only if clearly needed or when potential benefits outweigh potential hazards to the fetus.

Nursing Mothers: It is not known whether this drug is excreted in human milk. Because many drugs are excreted in human milk, caution should be exercised when this product is administered to a nursing woman.

Pediatric use: Safety and effectiveness in children under the age of 12 years have not been established.

ADVERSE REACTIONS:

In decreasing order of severity: skin irritation; occasional reports of increase in normal hair loss; discoloration of hair (can be avoided or minimized by thorough rinsing of hair after treatment). As with other shampoos, oiliness or dryness of hair and scalp may occur.

OVERDOSAGE:

There are no documented reports of serious toxicity in humans resulting from acute ingestion of this product. However, acute toxicity studies in animals suggest that ingestion of large amounts could result in potential human toxicity. Evacuation of the stomach contents should be considered in cases of acute oral ingestion.

DOSAGE AND ADMINISTRATION:

Shake well before use.

For seborrheic dermatitis and dandruff: Wet skin and apply to areas to be cleansed. Massage gently into the skin working into a full lather. Rinse thoroughly and pat dry. Generally, two applications each week for two weeks will control symptoms. Subsequently, shampoo may be used less frequently or as directed by a physician. It should not be applied more frequently than necessary to maintain control.

For tinea versicolor: Wet skin and apply to areas to be cleansed. Massage gently into the skin working into a full lather. Allow product to remain on skin for ten minutes, then rinse thoroughly and pat dry. Repeat procedure once a day for seven days or as directed by a physician.

STORAGE:

Store at 20°C to 25°C (68°F to 77°F), excursions permitted between 15°C to 30°C (between 59°F to 86°F). Brief exposure to temperatures up to 40°C (104°F) may be tolerated provided the mean kinetic temperature does not exceed 25°C (77°F); however, such exposure should be minimized.

NOTICE: Protect from freezing and excessive heat. The product may darken upon storage. Discoloration does not impair the efficacy or safety of the product. Keep container tightly closed.

HOW SUPPLIED:

This product is supplied in the following size(s):
6 fl. oz. (180 mL) bottles, NDC 52187-550-06

To report a serious adverse event or obtain product information, call 1-855-899-4237.

Distributed by:
KMM Pharmaceuticals, LLC
1000 N. West Street
Suite 1200, #1021
Wilmington, DE 19801
2100535 [00] Rev. 11/2021